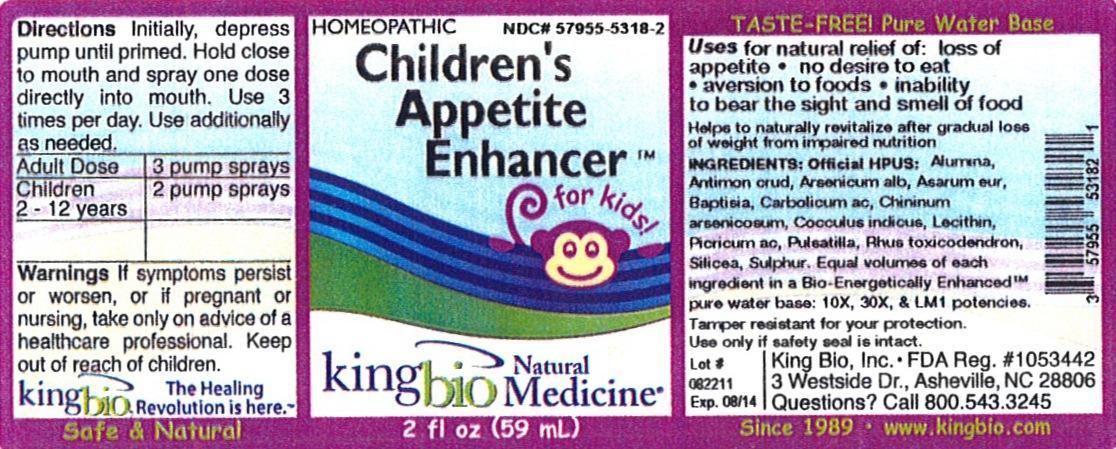 DRUG LABEL: Childrens Appetite Enhancer
NDC: 57955-5318 | Form: LIQUID
Manufacturer: King Bio Inc.
Category: homeopathic | Type: HUMAN OTC DRUG LABEL
Date: 20120904

ACTIVE INGREDIENTS: ALUMINUM OXIDE 10 [hp_X]/59 mL; ANTIMONY TRISULFIDE 10 [hp_X]/59 mL; ARSENIC TRIOXIDE 10 [hp_X]/59 mL; ASARUM EUROPAEUM 10 [hp_X]/59 mL; BAPTISIA TINCTORIA ROOT 10 [hp_X]/59 mL; PHENOL 10 [hp_X]/59 mL; QUININE ARSENITE 10 [hp_X]/59 mL; ANAMIRTA COCCULUS SEED 10 [hp_X]/59 mL; EGG PHOSPHOLIPIDS 10 [hp_X]/59 mL; PICRIC ACID 10 mL/59 mL; PULSATILLA VULGARIS 10 [hp_X]/59 mL; TOXICODENDRON PUBESCENS LEAF 10 [hp_X]/59 mL; SILICON DIOXIDE 10 [hp_X]/59 mL; SULFUR 10 [hp_X]/59 mL
INACTIVE INGREDIENTS: WATER

Children's Appetite Enhancer

Active Ingredients

Official HPUS: Alumina, Antimonium crudum, Arsenicum album, Asarum europaeum, Baptisia Tinctoria, Carbolicum acidum, Chininum arsenicosum, Cocculus indicus, Lecithin, Picricum acidum, Pulsatilla, Rhus toxicodendron, Silicea, and Sulphur.

Inactive Ingredient

Equal volumes of each ingredient in a Bio-Energetically Enhanced pure water base: 10X, 30X, and LM1 potencies.

Purpose

Uses for natural relief of:

- loss of appetite
- no desire to eat
- aversion to foods
- inability to bear the sight and smell of food

Helps to naturally revitalize after gradual loss of weight from impaired nutrition.

Directions

Initially, depress pump until primed. Hold close to mouth and spray one dose directly into mouth. Use 3 times per day. Use additionally as needed.

Adult Dose 3 pump sprays

Children 2-12 years 2 pump sprays

Warnings

If symptoms persist or worsen, or if pregnant or nursing, take only on advice of a healthcare professional. Keep out of reach of children.

Other: Tamper resistant for your protection. Use only if safety seal is intact.

Keep out of reach of children.

Indications and Usage

Uses for natural relief of: loss of appetite, no desire to eat, aversion to foods, inability to bear the sight and smell of food.

Helps to naturally revitalize after gradual loss of weight from impaired nutrition.

PACKAGE LABEL

King Bio Inc.

3 Westside Drive

Asheville, NC 28806

Question? Call 800.543.3245

www.kingbio.com